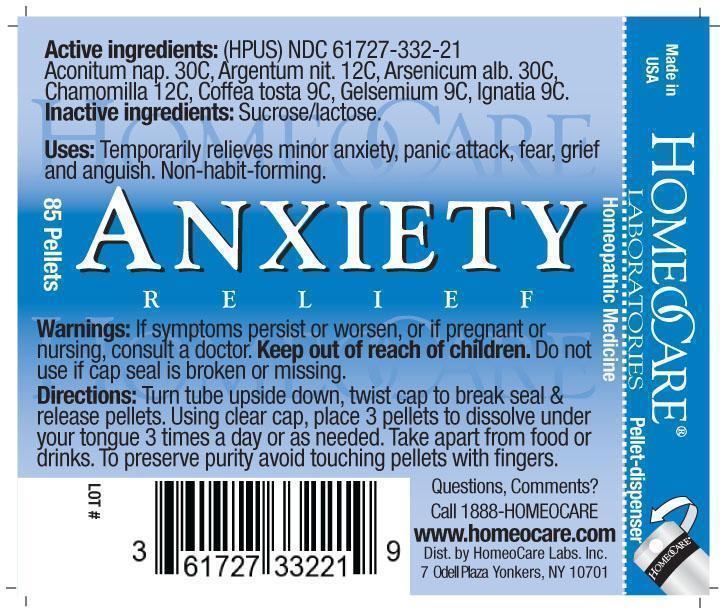 DRUG LABEL: Anxiety Relief
NDC: 61727-332 | Form: PELLET
Manufacturer: Homeocare Laboratories
Category: homeopathic | Type: HUMAN OTC DRUG LABEL
Date: 20181231

ACTIVE INGREDIENTS: ACONITUM NAPELLUS 30 [hp_C]/4 g; SILVER NITRATE 12 [hp_C]/4 g; ARSENIC TRIOXIDE 30 [hp_C]/4 g; MATRICARIA RECUTITA 12 [hp_C]/4 g; COFFEE BEAN 9 [hp_C]/4 g; GELSEMIUM SEMPERVIRENS ROOT 9 [hp_C]/4 g; STRYCHNOS IGNATII SEED 9 [hp_C]/4 g
INACTIVE INGREDIENTS: SUCROSE; LACTOSE

Anxiety Relief

Active Ingredients:

(HPUS) Aconitum nap. 30C, Argentum nit. 12C, Arsenicum alb. 30C, Chamomilla 12C, Coffea Tosta 9C, Gelsemium 9C, Ignatia 9C.

Purpose:

Temporarily relieves minor anxiety, panic attack, fear, grief, and anguish, Non-habit forming.

Keep out of reach of children.

Uses:

Temporarily relieves minor anxiety, panic attack, fear, grief and anguish. Non-habit forming.

Warnings:

If symptoms persist or worsen, or if pregnant or nursing, consult a doctor. Keep out of reach of children. Do not use if cap seal is broken or missing.

Inactive Ingredients:

Sucrose/lactose.

Dosage and Administration:

Turn tube upside down, twist cap to break seal & release pellets. Using clear cap, place 3 pellets to dissolve under your tongue 3 times a day as needed. Take apart from food or drinks. To preserve purity avoid touching pellets with fingers.

Anxiety Relief

anxiety relief image

hcl_label_anxiety 2012.jpg